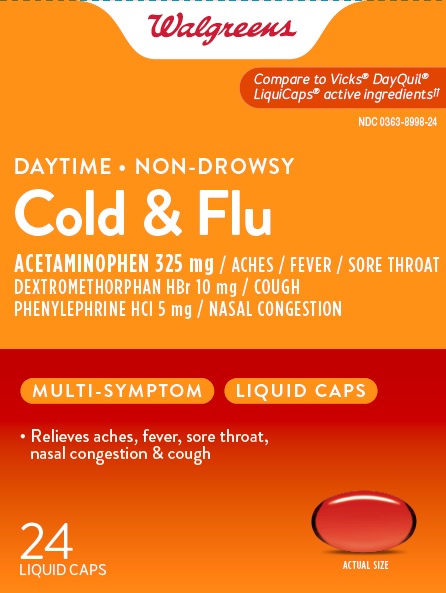 DRUG LABEL: Daytime Non-Drowsy Cold and Flu
NDC: 0363-8998 | Form: CAPSULE, LIQUID FILLED
Manufacturer: Walgreens Company
Category: otc | Type: HUMAN OTC DRUG LABEL
Date: 20260119

ACTIVE INGREDIENTS: ACETAMINOPHEN 325 mg/1 1; DEXTROMETHORPHAN HYDROBROMIDE 10 mg/1 1; PHENYLEPHRINE HYDROCHLORIDE 5 mg/1 1
INACTIVE INGREDIENTS: FD&C RED NO. 40; GELATIN; GLYCERIN; POLYETHYLENE GLYCOL 400; POVIDONE K30; PROPYLENE GLYCOL; WATER; SORBITOL; SORBITAN; TITANIUM DIOXIDE; FD&C YELLOW NO. 6

Walgreens Non-Drowsy Daytime Cold & Flu

Drug Facts

ACTIVE INGREDIENT

Active ingredients (in each softgel) | Purpose
Acetaminophen 325 mg | Pain reliever/fever reducer
Dextromethorphan Hydrobromide 10 mg | Cough suppressant
Phenylephrine HCl 5 mg | Nasal decongestant

Uses

temporarily relieves common cold/flu symptoms:

- nasal congestion
- cough due to minor throat & bronchial irritation
- sore throat
- headache
- minor aches/pains
- fever

Warnings

Liver warning

This product contains acetaminophen. Severe liver damage may occur if you take:

- more than 4 doses in 24 hours, which is the maximum daily amount for this product
- with other drugs containing acetaminophen
- 3 or more alcoholic drinks every day while using this product

Sore throat warning

If sore throat is severe, lasts for more than 2 days, occurs with or is followed by fever, headache, rash, nausea, or vomiting, see a doctor promptly.

Do not use:

- with any other drug containing acetaminophen (prescription or nonprescription). If you are not sure whether a drug contains acetaminophen, ask a doctor or pharmacist.
- If you are now taking a prescription monoamine oxidase inhibitor (MAOI) (certain drugs for depression, psychiatric or emotional conditions, or Parkinson's disease), or for 2 weeks after stopping the MAOI drug. If you do not know if your prescription drug contains an MAOI, ask a doctor or pharmacist before taking this product.

Ask a doctor before use if you have

- liver disease
- heart disease
- thyroid disease
- diabetes
- high blood pressure
- trouble urinating due to enlarged prostate gland
- cough that occurs with too much phlegm (mucus)
- persistent or chronic cough as occurs with smoking, asthma, or emphysema

Ask a doctor or pharmacist before use if you are taking the blood-thinning drug Warfarin.

When using this product

- do not use more than directed.

Stop use and ask a doctor if

- you get nervous, dizzy, or sleepless
- symptoms get worse or last more than 5 days (children) or 7 days (adults)
- fever gets worse or lasts more than 3 days
- redness or swelling is present
- new symptoms occur
- cough comes back, or occurs with rash or headache that lasts

These could be signs of a serious condition.

PREGNANCY OR BREAST FEEDING

If pregnant or breast-feeding, ask a health professional before use.

Keep out of reach of children.

Overdose warning

Taking more than directed can cause serious health problems. In case of overdose, get medical help or contact a Poison Control Center right away. Quick medical attention is critical for adults and for children, even if you do not notice any signs or symptoms.

Directions

- Take only as directed—see Overdose warning.
- do not exceed 4 doses per 24 hours.

adults and children 12 years of age and over | swallow 2 softgels with water every 4 hours
children 4 to under 12 years of age | ask a doctor
children under 4 years of age | do not use

When using other Daytime or Nighttime products, carefully read each label to ensure correct dosing

Other information

- store at room temperature 15°-30°C (59°-86°F) and avoid excessive heat

Inactive ingredients

FD&C Red# 40, FD&C Yellow# 6, gelatin, glycerin, polyethylene glycol, povidone, propylene glycol, purified water, sorbitol sorbitan, titanium dioxide

Questions or comments?

1-888-333-9792

PRINCIPAL DISPLAY PANEL

COMPARE TO
VICKS ® DAYQUIL ®LiquiCaps® ACTIVE INGREDIENTS††

Walgreens

DAYTIME NON-DROWSY

Cold & Flu

Acetaminophen325mg/ ACHES/ FEVER/ SORE THROAT
Dextromethorphan HBr 10mg/ COUGH
Phenylephrine HCl5mg/ NASAL CONGESTION
Relieves aches, fever, sore throat, nasal congestion & cough

Actual Size

24 softgels

†† This product is not manufactured or distributed by
Procter & Gamble, owner of the registered
trademarks Vicks® DayQuil® LiquiCaps®.